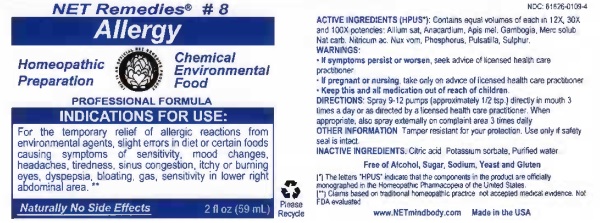 DRUG LABEL: Allergy
NDC: 61626-0109 | Form: LIQUID
Manufacturer: Net Remedies
Category: homeopathic | Type: HUMAN PRESCRIPTION DRUG LABEL
Date: 20210121

ACTIVE INGREDIENTS: GARLIC 12 [hp_X]/59.1 mL; ANACARDIUM OCCIDENTALE FRUIT 12 [hp_X]/59.1 mL; APIS MELLIFERA 12 [hp_X]/59.1 mL; GAMBOGE 12 [hp_X]/59.1 mL; MERCURIUS SOLUBILIS 12 [hp_X]/59.1 mL; SODIUM CARBONATE 12 [hp_X]/59.1 mL; NITRIC ACID 12 [hp_X]/59.1 mL; STRYCHNOS NUX-VOMICA SEED 12 [hp_X]/59.1 mL; PHOSPHORUS 12 [hp_X]/59.1 mL; ANEMONE PULSATILLA 12 [hp_X]/59.1 mL; SULFUR 12 [hp_X]/59.1 mL
INACTIVE INGREDIENTS: CITRIC ACID MONOHYDRATE; POTASSIUM SORBATE; WATER

Allergy

ACTIVE INGREDIENT

ACTIVE INGREDIENTS (HPUS*): Contains equal volumes of each in 12X, 30X, and 100X potencies: Allium sat, Anacardium, Apis mel, Gambogia, Merc solub, Nat carb, Nitricum ac, Nux vom, Phosphorus, Pulsatilla, Sulphur.

(*) The letters "HPUS" indicate that the components in the product are offically monographed in the Homeopathic Pharmacopeia of the United States.

(**) Claims based on traditional homeopathic practice, not accepted medical evidence. Not FDA evaluated.

INDICATIONS AND USAGE

INDICATIONS FOR USE: For the temporary relief of allergic reactions from environmental agents, slight errors in diet or certain foods causing symptoms of sensitivity, mood changes, headaches, tiredness, sinus congestion, itchy or burning eyes, dyspepsia, bloating, gas, sensitivity in lower right abdominal area.**

WARNINGS:

• If symptoms persist or worsen, seek advice of licensed health care practitioner.

• If pregnant or nursing, take on only advice of licensed health care practitioner.

• Keep this and all medication out of reach of children.

KEEP OUT OF REACH OF CHILDREN

• Keep this and all medication out of reach of children.

DOSAGE AND ADMINISTRATION

DIRECTIONS: Spray 9-12 pumps (approximately 1/2 tsp.) directly in mouth 3 times a day or as directed by a licensed health care practitioner. When appropriate, also spray externally on complaint area 3 times daily.

OTHER INFORMATION: Tamper resistant for your protection. Use only if safe seal is intact.

INACTIVE INGREDIENTS: Citric acid, Potassium sorbate, Purified water.

Free of Alcohol, Sugar, Sodium, Yeast and Gluten.

QUESTIONS

www.NETmindbody.com

Made in the USA.

PACKAGE LABEL

NET Remedies #8

Allergy

Homeopathic Preparation

Chemical Environmental

FoodPROFESSIONAL FORMULA

Naturally No Side Effects:

PURPOSE

INDICATIONS FOR USE: For the temporary relief of allergic reactions from environmental agents, slight errors in diet or certain foods causing symptoms of sensitivity, mood changes, headaches, tiredness, sinus congestion, itchy or burning eyes, dyspepsia, bloating, gas, sensitivity in lower right abdominal area.**